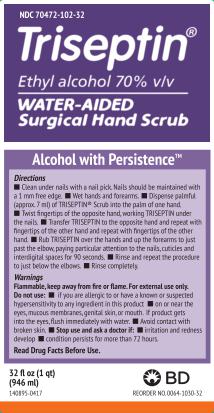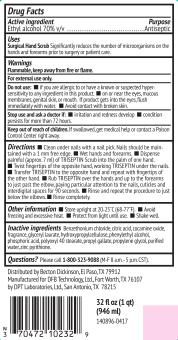 DRUG LABEL: TRISEPTIN

NDC: 70472-102 | Form: LOTION
Manufacturer: DFB Technology Ltd
Category: otc | Type: HUMAN OTC DRUG LABEL
Date: 20170912

ACTIVE INGREDIENTS: ALCOHOL 0.7 mL/1 mL
INACTIVE INGREDIENTS: BENZETHONIUM CHLORIDE; CITRIC ACID MONOHYDRATE; COCAMINE OXIDE; GLYCERYL LAURATE; HYDROXYPROPYL CELLULOSE; PHENYLETHYL ALCOHOL; PHOSPHORIC ACID; POLYOXYL 40 STEARATE; PROPYL GALLATE; PROPYLENE GLYCOL; WATER; PYRITHIONE ZINC

TRISEPTIN® Water-Aided Surgical Hand Scrub

Drug Facts

Active ingredient

Ethyl Alcohol 70% v/v

Purpose

Antiseptic

Uses

Surgical Hand Scrub Significantly reduces the number of microorganisms on the hands and forearms prior to surgery or patient care.

Warnings

Flammable, keep away from fire or flame.
For external use only.

Do not use:

- if you are allergic to or have a known or suspected hypersensitivity to any ingredient in this product.
- on or near the eyes, mucous membranes, genital skin, or mouth. If product gets into the eyes, flush immediately with water.
- Avoid contact with broken skin.

Stop use and ask doctor if:

- irritation and redness develop
- condition persists for more than 72 hours

Keep out of reach of children.

If swallowed, get medical help or contact a Poison Control Center right away.

Directions

- Clean under nails with a nail pick. Nails should be maintained with a 1 mm free edge.
- Wet hands and forearms.
- Dispense palmful (approx. 7 ml) of TRISEPTIN Scrub into the palm of one hand.
- Twist fingertips of the opposite hand, working TRISEPTIN under the nails.
- Transfer TRISEPTIN to the opposite hand and repeat with fingertips of the other hand.
- Rub TRISEPTIN over the hands and up the forearms to just past the elbow, paying particular attention to the nails, cuticles and interdigital spaces for 90 seconds.
- Rinse and repeat the procedure to just below the elbows.
- Rinse completely.

Other information

- Store upright at 20-25°C (68-77°F).
- Avoid freezing and excessive heat.
- Protect from light until use.
- Shake well.

Inactive ingredients

Benzethonium chloride, citric acid, cocamine oxide, fragrance, glyceryl laurate, hydroxypropylcellulose, phenylethyl alcohol, phosphoric acid, polyoxyl 40 stearate, propyl gallate, propylene glycol, purified water, zinc pyrithione.

Questions?

Please call 1-800-323-9088 (M-F 8 a.m.-5 p.m. CST).

Distributed by Becton Dickinson, El Paso, TX 79912
Manufactured for DFB Technology, Ltd., Fort Worth, TX 76107
by DPT Laboratories, Ltd., San Antonio, TX 78215

32 fl oz (1 qt)

(946 ml)
140896-0417

PRINCIPAL DISPLAY PANEL

NDC 70472-102-32

Triseptin®
Ethyl alcohol 70% v/v
WATER-AIDED
Surgical Hand Scrub

Alcohol with Persistence™

Directions

- Clean under nails with a nail pick. Nails should be maintained with a 1 mm free edge.
- Wet hands and forearms.
- Dispense palmful (approx. 7 ml) of TRISEPTIN® Scrub into the palm of one hand.
- Twist fingertips of the opposite hand, working TRISEPTIN under the nails.
- Transfer TRISEPTIN to the opposite hand and repeat with fingertips of the other hand.
- Rub TRISEPTIN over the hands and up the forearms to just past the elbow, paying particular attention to the nails, cuticles and interdigital spaces for 90 seconds.
- Rinse and repeat the procedure to just below the elbows.
- Rinse completely.

Warnings
Flammable, keep away from fire or flame.
For external use only.
Do not use:

- if you are allergic to or have a known or suspected hypersensitivity to any ingredient in this product.
- or on or near the eyes, mucous membranes, genital skin, or mouth. If product gets into the eyes, flush immediately with water.
- Avoid contact with broken skin.

Stop use and ask doctor if:

- irritation and redness develop
- condition persists for more than 72 hours.

Read Drug Facts Before Use.

32 fl oz (1 qt)

(946 ml)
140895-0417

BD

REORDER NO. 0064-1030-32

PACKAGE LABEL.PRINCIPAL DISPLAY PANEL